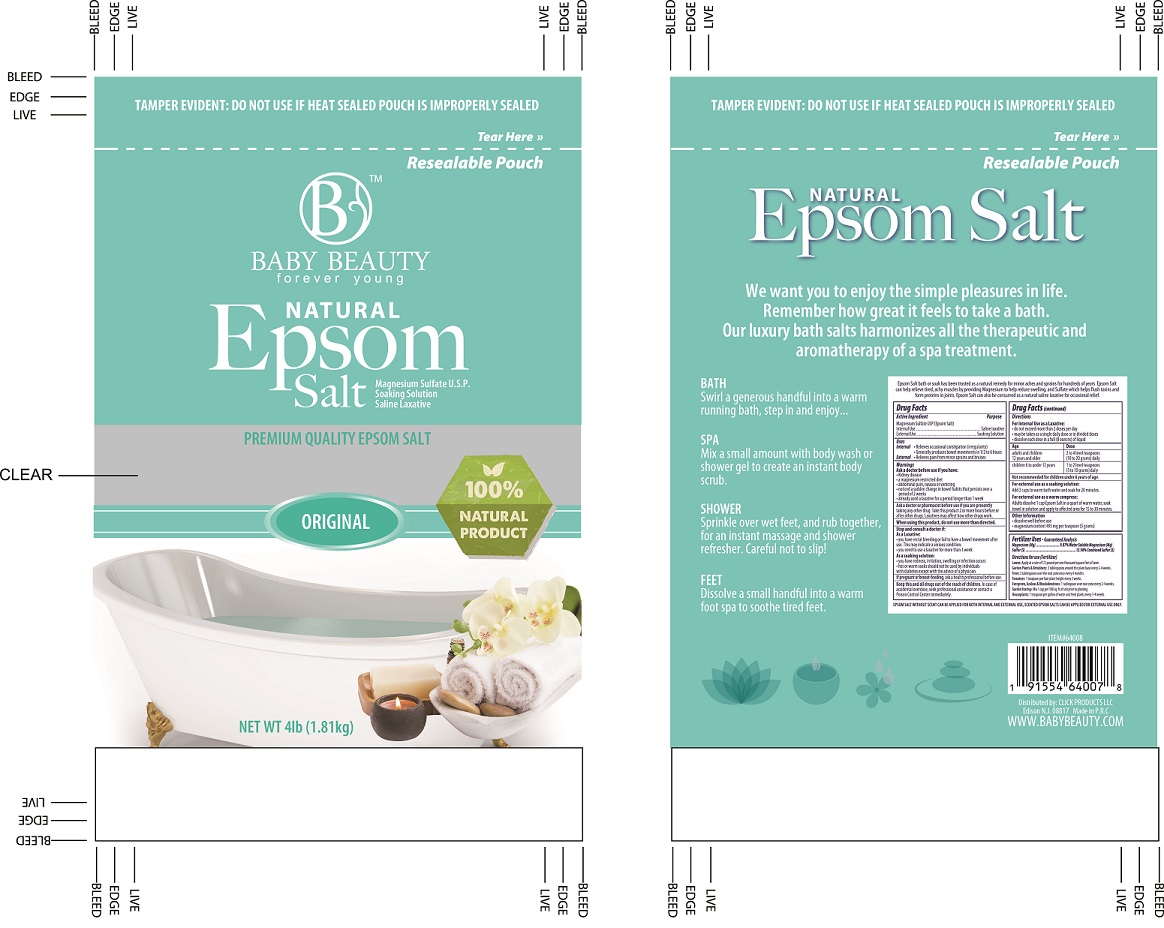 DRUG LABEL: Epsom Salt
NDC: 71611-010 | Form: GRANULE
Manufacturer: Click Products LLC
Category: otc | Type: HUMAN OTC DRUG LABEL
Date: 20200323

ACTIVE INGREDIENTS: MAGNESIUM SULFATE, UNSPECIFIED 100 g/100 g
INACTIVE INGREDIENTS: WATER

ACTIVE INGREDIENT

Magnesium Sullfate USP (Epsom Salt)

PURPOSE

Internal Use ...............Saline laxative

External Use ..............Soaking Solution

DOSAGE AND ADMINISTRATION

For internal Use as laxative:

- do not exceed more than 2 doses per day
- may be taken as a single daily dose or in divided doses
- dissolve each dose in a full (8 ounces)of liquid
- Age = Aduls and children 12 years and older ............Dose: 2 to 4 level teaspoons (10 to 22 grams) daily
- Children 6 and under 12 years....................................Dose: 1 to 2 level teaspoons (5 to 10 grams) daily
- Not recommended for children under 6 years of age.

USES

Internal

- Relieves occasional constipation (irregularity)
- Generally produces bowel movements in 1/2 to 6 hours

External - RElieves pain from minor prains and bruises

KEEP OUT OF REACH OF CHILDREN. Where prompt relief is not obtained or where ther is evidence of infection, discontinue use and consult a physician. Hot or warm soaks should not be used by individuals with diabetes except on advice of a physician. Avoid contact with eyes.

WARNINGS

Warnings - Ask a doctor before use if you have:

- kidney disease
- a magnesium restricted diet
- abdominal pain, nausea or vomiting
- noticed a sudden change in bowel habits that persists over a period of 2 weeks
- already used a laxative for a period longer than 1 week

Ask doctor or pharmacist before use if you are presently taking any other drug. take this product 2 or more hours before or after other drugs. Laxatives may affect how other drugs work.

When using this product, do not use more than directed.

Stop and consult a doctor if:

- As laxative: you have rectal bleeding or fail to have a bowel movement after use.
- This may indicate a serious condition
- You need to use a laxative for more than 1 week.

As a soaking solution if:

- you have redness, irritation, swelling or infection occurs
- hot or warm soaks should not be used by individuals with diabeted except with the advise of a pyhsician.

If pregnant or breast-feedig , ask a health professional before use.

Keep this and all drugs out of the reach of children. In case of accidental overdose, seek professional assistance or contact a poison control center immediately.

EPSOM SALT WITHOUT SCENT CAN BE APPLIED FOR BOTH INTERNAL AND EXTERNAL USE, SCENTED EPSOM SALT CAN BE APPLIED FOR EXTERNAL USE ONLY.

INACTIVE INGREDIENT

n/a